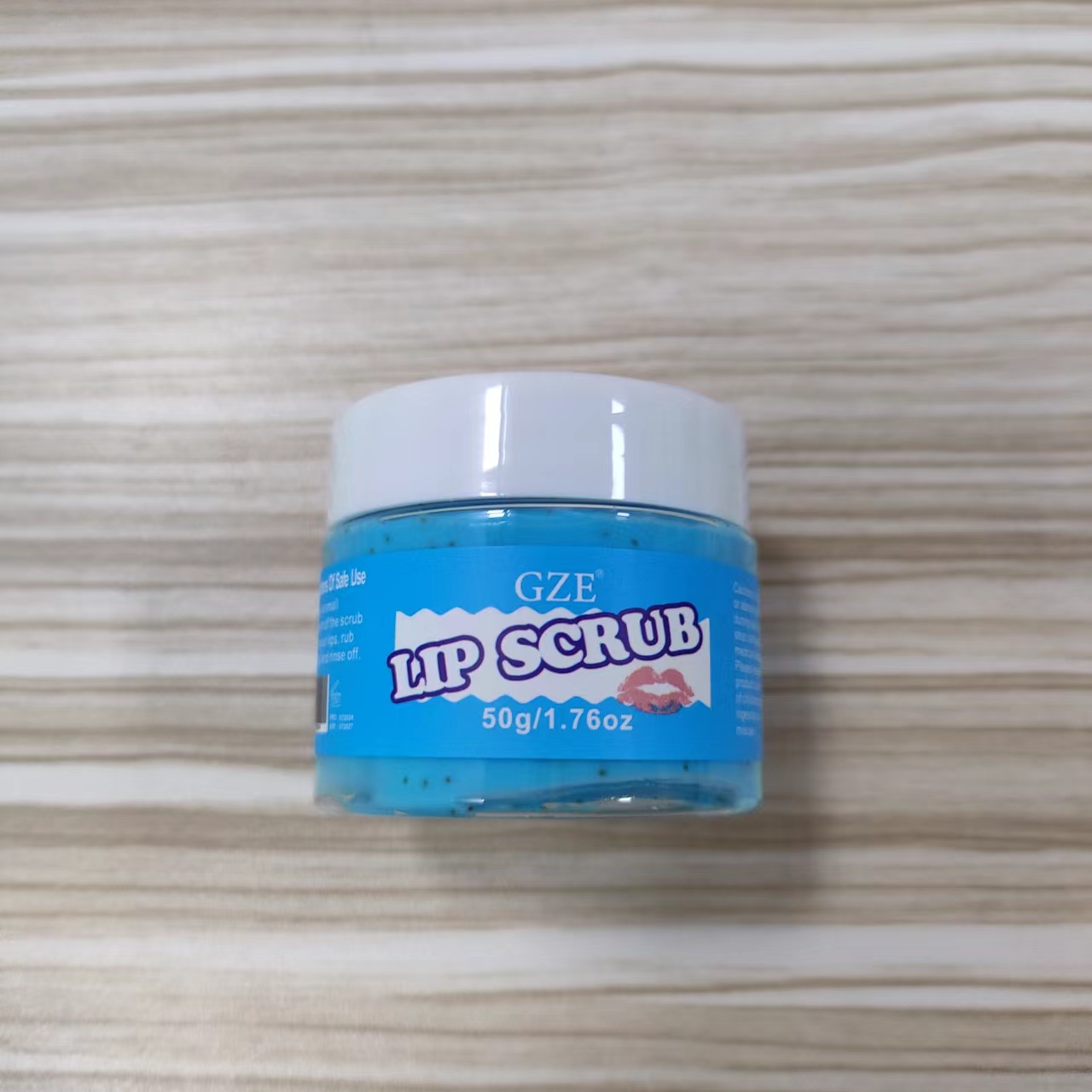 DRUG LABEL: GZE LIP SCRUB
NDC: 74458-296 | Form: CREAM
Manufacturer: Guangzhou Yilong Cosmetics Co., Ltd
Category: otc | Type: HUMAN OTC DRUG LABEL
Date: 20241111

ACTIVE INGREDIENTS: COCOS NUCIFERA (COCONUT) OIL 10 g/100 g; SIMMONDSIA CHINENSIS SEED 10 g/100 g
INACTIVE INGREDIENTS: PRUNUS AMYGDALUS DULCIS (SWEET ALMOND) OIL; AQUA; TOCOPHEROL; GLYCERIN

GZE LIP SCRUB

ACTIVE INGREDIENT

Cocos Nucifera (Coconut) Oil

Simmondsia Chinensis (Jojoba) Seed Powder

INACTIVE INGREDIENT

Aqua

Glycerin

Tocopherol

Prunus Amygdalus Dulcis (Sweet Almond) Oil

PURPOSE

Lip Exfoliation.

INDICATIONS AND USAGE

Apply a small amount of the scrub onto your lips, rub gently and rinse off.

WARNINGS

For external use only.

Stop use and ask a doctor if rash occurs.

Do not use on damaged or broken skin.

When using this product keep out of eyes. Rinse with water to remove.

Keep out of reach of children. If swallowed, get medical help or contact a Poison Control Center right away.

DOSAGE AND ADMINISTRATION

Apply a small amount of the scrub onto your lips, rub gently and rinse off.